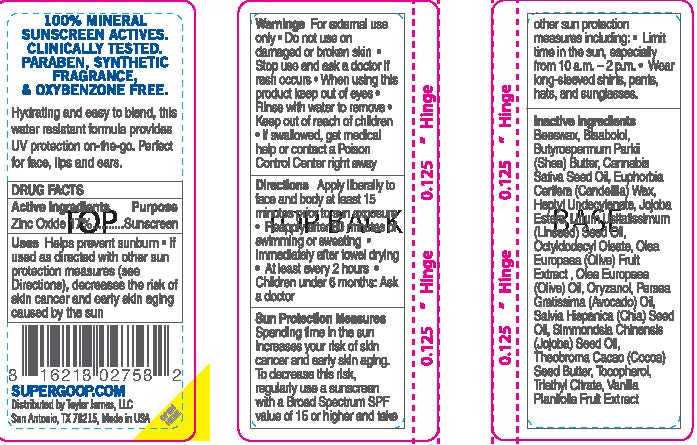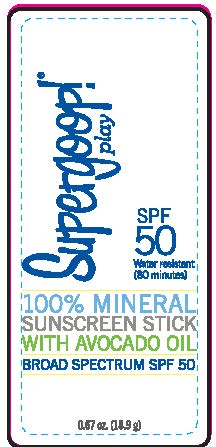 DRUG LABEL: Mineral Sunscreen Stick SPF 50

NDC: 75936-511 | Form: STICK
Manufacturer: TAYLOR JAMES, LTD.
Category: otc | Type: HUMAN OTC DRUG LABEL
Date: 20211011

ACTIVE INGREDIENTS: ZINC OXIDE 17 g/100 g
INACTIVE INGREDIENTS: YELLOW WAX; LEVOMENOL; SHEA BUTTER; CANNABIS SATIVA SEED OIL; CANDELILLA WAX; HEPTYL UNDECYLENATE; JOJOBA OIL, RANDOMIZED; LINSEED OIL; OCTYLDODECYL OLEATE; BLACK OLIVE; OLIVE OIL; GAMMA ORYZANOL; AVOCADO OIL; CHIA SEED OIL; JOJOBA OIL; COCOA BUTTER; TOCOPHEROL; TRIETHYL CITRATE; VANILLA

Mineral Sunscreen Stick SPF 50

Active Ingredients Purpose

Zinc Oxide 17% ............... Sunscreen

Uses

Helps prevent sunburn

- If used as directed with other sun protection measures (see Directions), decreases the risk of skin cancer and early skin aging caused by the sun

Keep out of reach of children

Stop use and ask a doctor if rash occurs

Warnings

For external use only

- Do not use on damaged or broken skin
- When using this product keep out of eyes
- Rinse with water to remove
- If swallowed, get medical help or contact a Poison Control Center right away

Directions

- Apply liberally to face and body at least 15 minutes prior to sun exposure
- Reapply after 80 minutes of swimming or sweating
- Immediately after towel drying
- At least every 2 hours
- Chlidren under 6 months: Ask a doctor

Sun Protection Measures

Spending time in the sun increases your risk of skin cancer and early skin aging. To decrease this risk, regularly use a sunscreen with a Broad Spectrum SPF value of 15 or higher and take other sun protection measures including:

- Limit time in the sun, especially from 10a.m.-2p.m.
- Wear long-sleeved shirts, pants, hats, and sunglasses

Inactive Ingredients

Beeswax, Bisabolol,

Butyrospermum Parkii (Shea) Butter, Cannabis Sativa Seed Oil, Euphorbia Cerifera (Candelilla) Wax, Heptyl Undecylenate, Jojoba Esters, Linum Usitatissimum (Linseed) Seed Oil, Octyldodecyl Oleate, Olea Europaea (Olive) Fruit Extract, Olea Europaea (Olive) Oil, Oryzanol, Persea Gratissima (Avocado) Oil, Salvia Hispanica (Chia) Seed Oil, Simmondsia Chinensis (Jojoba) Seed Oil, Theobroma Cocao (Cocoa) Seed Butter, Tocopherol, Triethyl Citrate, Vanilla Planifolia Fruit Extract

PACKAGE LABEL

Supergoop

SPF 50

Water resistant (80 minutes)

100% Mineral Sunscreen Stick

With Avocado Oil

Broad Spectrum SPF 50